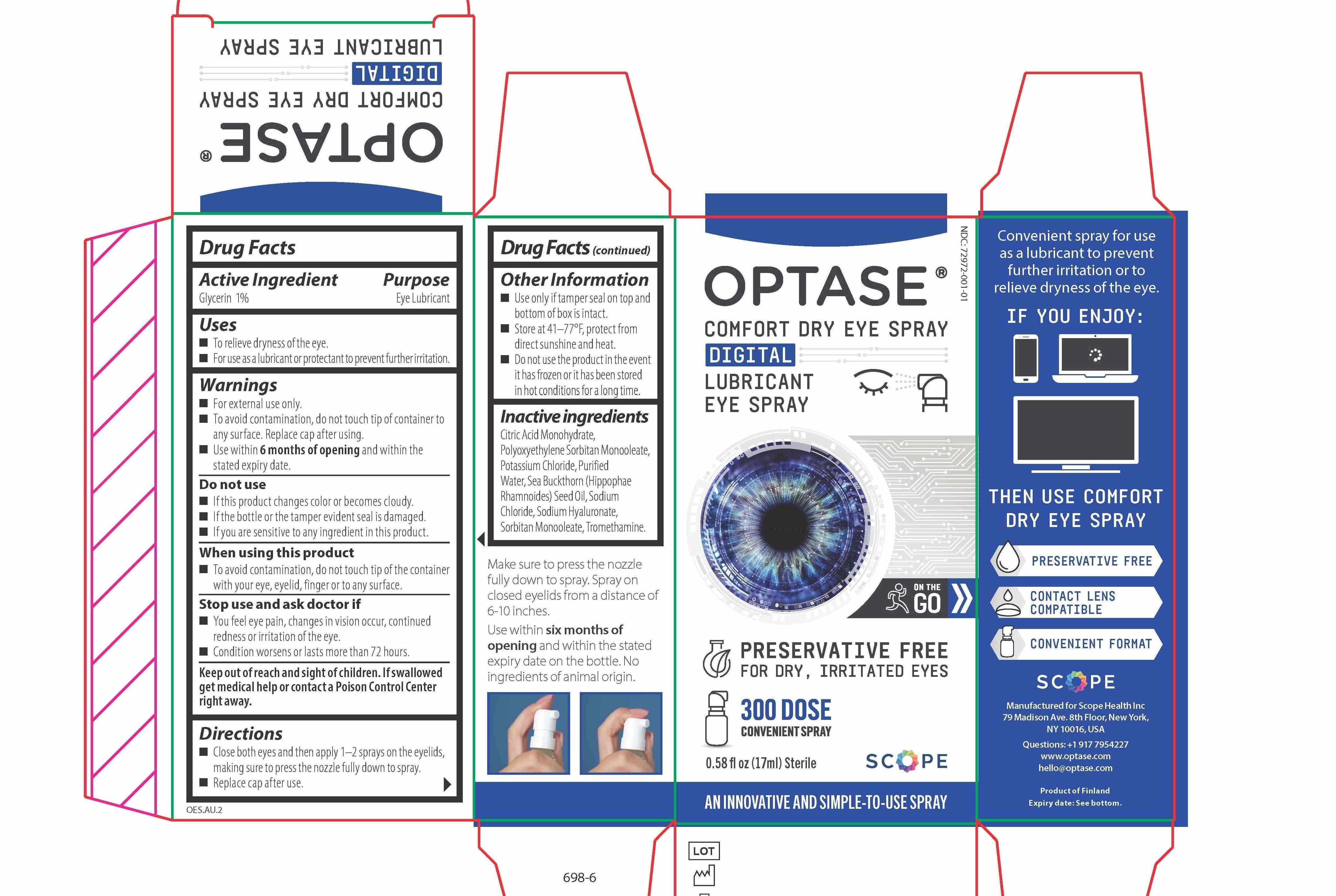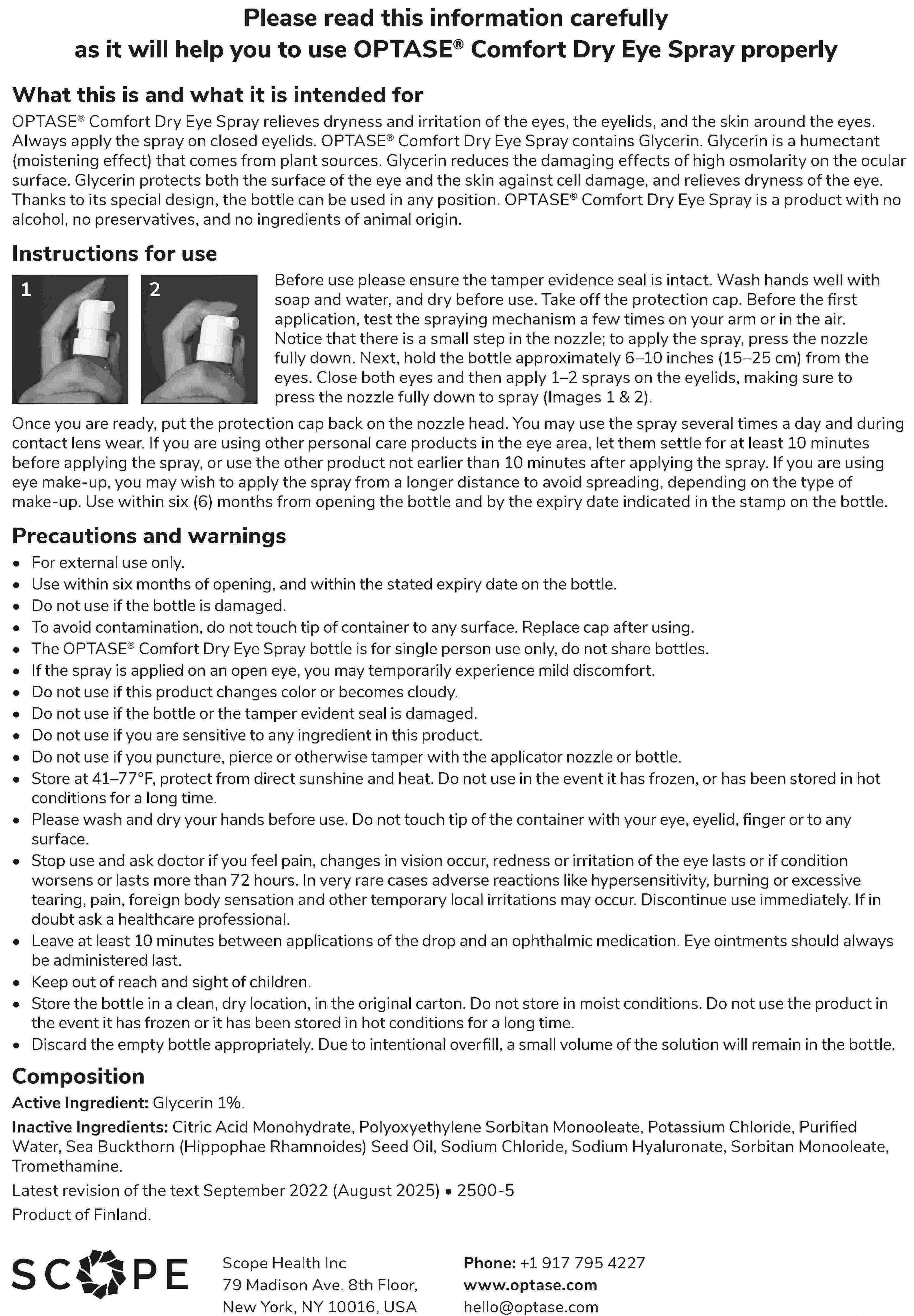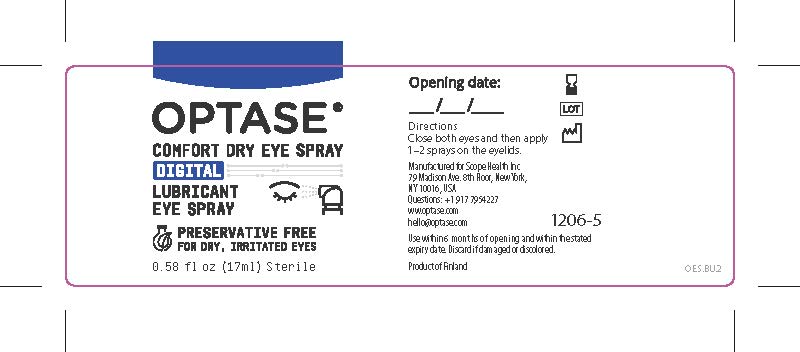 DRUG LABEL: Optase
NDC: 72972-001 | Form: SPRAY
Manufacturer: Scope Health Inc
Category: otc | Type: HUMAN OTC DRUG LABEL
Date: 20260129

ACTIVE INGREDIENTS: GLYCERIN 1 mg/1 mL
INACTIVE INGREDIENTS: SODIUM CHLORIDE; WATER; HYALURONATE SODIUM; POLYSORBATE 80; SORBITAN MONOOLEATE; TROMETHAMINE; POTASSIUM CHLORIDE; CITRIC ACID MONOHYDRATE; HIPPOPHAE RHAMNOIDES SEED OIL

Optase Comfort Dry Eye Spray

PURPOSE

Eye Lubricant

Warning
• For external use only.

- To avoid contamination, do not touch tip of container to any surface. Replace cap after using.

• If solution changes color or becomes cloudy, do not use.
Stop use and ask doctor if
• You feel eye pain.
• Changes in vision occur.
• Redness or irritation of the eye lasts.
• Condition worsens or lasts more than 72 hours

INDICATIONS AND USAGE

• To relieve dryness of the eye
• For use as a lubricant or protectant to prevent further irritation.

DOSAGE AND ADMINISTRATION

- Close both eyes then apply 1-2 sprays on the eyelids making sure to press the nozzle fully down to spray.
- Replace cap after use.

INACTIVE INGREDIENT

Citric Acid Monohydrate, Polyoxyethylene Sorbitan Monoleate, Potassium Chloride, Purified Water, Sea Buckthorn Seed Oil, Sodium Chloride, Sodium Hyaluronate, Sorbitan Monoleate, Tromethamine.

ACTIVE INGREDIENT

Glycerin 1%

Keep Out of Reach and Sight of Children

If swallowed, get medical help or contact a poison control center right away.